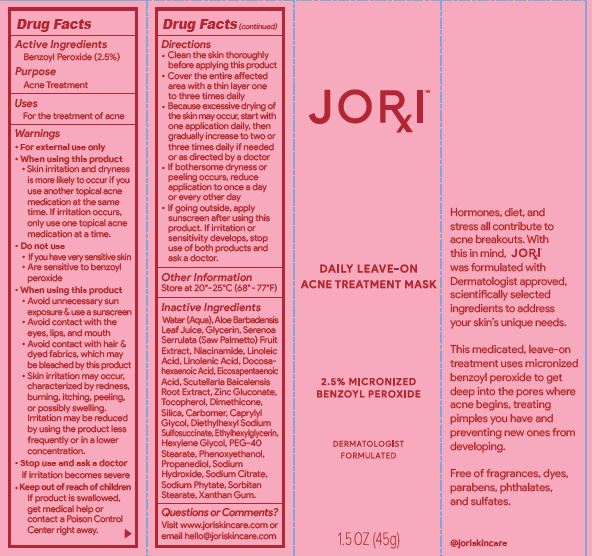 DRUG LABEL: Daily Leave on Acne Treatment Mask
NDC: 62742-4212 | Form: CREAM
Manufacturer: Allure Labs
Category: otc | Type: HUMAN OTC DRUG LABEL
Date: 20241209

ACTIVE INGREDIENTS: BENZOYL PEROXIDE 25 mg/1 g
INACTIVE INGREDIENTS: WATER; LINOLENIC ACID; SODIUM HYDROXIDE; SORBITAN MONOSTEARATE; PHYTATE SODIUM; HEXYLENE GLYCOL; PROPANEDIOL; GLYCERIN; ALOE VERA LEAF; DOCONEXENT; SAW PALMETTO; NIACINAMIDE; ICOSAPENT; DIMETHICONE; SILICON DIOXIDE; PEG-40 STEARATE; SODIUM CITRATE; XANTHAN GUM; ETHYLHEXYLGLYCERIN; LINOLEIC ACID; ZINC GLUCONATE; CARBOMER HOMOPOLYMER, UNSPECIFIED TYPE; DOCUSATE SODIUM; SCUTELLARIA BAICALENSIS ROOT; TOCOPHEROL; CAPRYLYL GLYCOL; PHENOXYETHANOL

Drug Facts

Active Ingredients
Benzoyl Peroxide 2.5%

Purpose
Acne Treatment

Uses
For the treatment of acne

Warnings
For external use only

Do not use
If you have very sensitive skin
Are sensitive to benzoyl
peroxide

When using this product
• Avoid unnecessary sun
exposure & use a sunscreen
• Avoid contact with the
eyes, lips, and mouth
• Avoid contact with hair &
dyed fabrics, which may
be bleached by this product
• Skin irritation may occur,
characterized by redness,
burning, itching, peeling,
or possibly swelling.
Irritation may be reduced
by using the product less
frequently or in a lower
concentration.

Stop use and ask a doctor
If irritation becomes severe

Keep out of reach of children
If product is swallowed,
get medical help or
contact a Poison Control
Center right away.

Directions
• Clean the skin thoroughly
before applying this product
• Cover the entire affected
area with a thin layer one
to three times daily
• Because excessive drying of
the skin may occur, start with
one application daily, then
gradually increase to two or
three times daily if needed
or as directed by a doctor
• If bothersome dryness or
peeling occurs, reduce
application to once a day
or every other day
• If going outside, apply
sunscreen after using this
product. If irritation or
sensitivity develops, stop
use of both products and
ask a doctor.

Other Information
Store at 20°- 25°C (68° - 77°F)

Inactive Ingredients
Water (Aqua), Aloe Barbadensis
Leaf Juice, Glycerin, Serenoa
Serrulata (Saw Palmetto) Fruit
Extract, Niacinamide, Linoleic
Acid, Linolenic Acid, Docosahexaenoic
Acid, Eicosapentaenoic
Acid, Scutellaria Baicalensis
Root Extract, Zinc Gluconate,
Tocopherol, Dimethicone,
Silica, Carbomer, Caprylyl
Glycol, Diethylhexyl Sodium
Sulfosuccinate, Ethylhexylglycerin,
Hexylene Glycol, PEG-40
Stearate, Phenoxyethanol,
Propanediol, Sodium
Hydroxide, Sodium Citrate,
Sodium Phytate, Sorbitan
Stearate, Xanthan Gum.